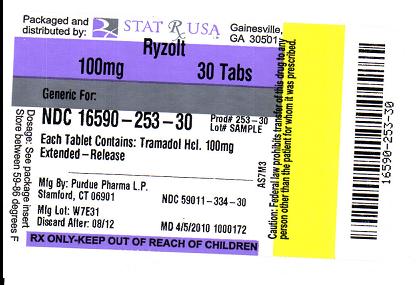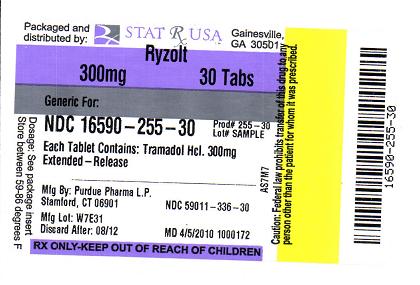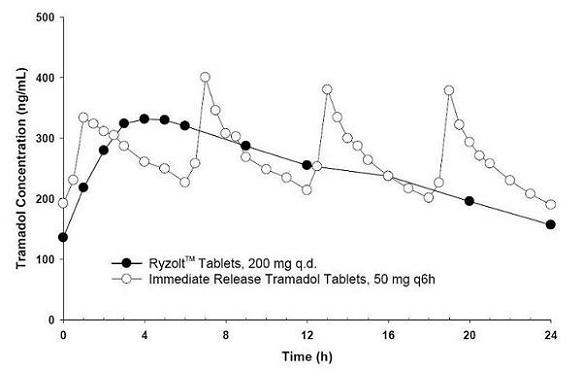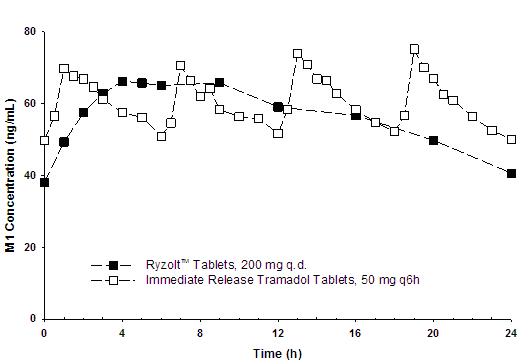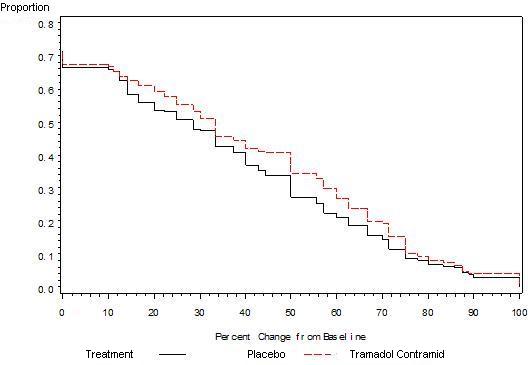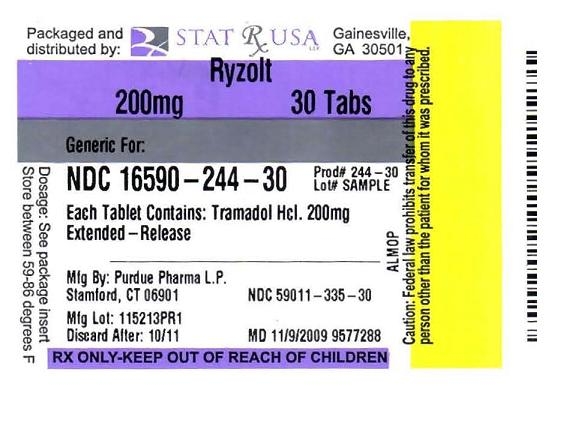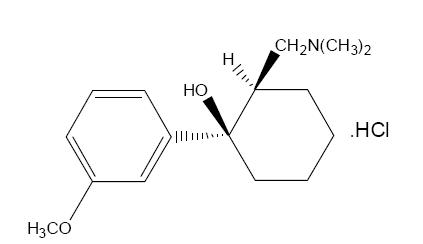 DRUG LABEL: RYZOLT
NDC: 16590-244 | Form: TABLET, EXTENDED RELEASE
Manufacturer: Stat Rx USA
Category: prescription | Type: HUMAN PRESCRIPTION DRUG LABEL
Date: 20101119

ACTIVE INGREDIENTS: TRAMADOL HYDROCHLORIDE 200 mg/1 1
INACTIVE INGREDIENTS: SILICON DIOXIDE; MAGNESIUM STEARATE; POVIDONE; SODIUM LAURYL SULFATE; XANTHAN GUM

RYZOLT (tramadol hydrochloride) tablet, extended release

DESCRIPTION

RYZOLT™
(tramadol hydrochloride extended-release tablets) DescriptionRYZOLT™ (tramadol hydrochloride extended-release tablets) is a centrally acting analgesic composed of a dual-matrix delivery system with both immediate-release and extended-release characteristics. The chemical name for tramadol hydrochloride is (±)cis-2-[(dimethylamino) methyl]-1-(3-methoxyphenyl) cyclohexanol hydrochloride. Its structural formula is:

C16H25NO2 ·HCl

The molecular weight of tramadol hydrochloride is 299.8. Tramadol hydrochloride is a white crystalline powder that is freely soluble in water and ethanol. RYZOLT™ extended-release tablets are for oral administration and contain 100 mg, 200 mg or 300 mg of tramadol hydrochloride. The tablets are white to off-white in color. The inactive ingredients in the tablet are colloidal silicon dioxide, pregelatinized modified starch, hydrogenated vegetable oil, magnesium stearate, polyvinyl acetate, povidone, sodium lauryl sulfate and xanthan gum.

Clinical Pharmacology Mechanism of Action

RYZOLT™ is a centrally acting synthetic opioid analgesic. Although its mode of action is not completely understood, at least two complementary mechanisms that demonstrate three different types of activity appear applicable: binding of parent and M1 metabolite to µ-opioid receptors and weak inhibition of reuptake of norepinephrine and serotonin.

Opioid activity is due to both low affinity binding of the parent compound and higher affinity binding of the O-demethylated metabolite (M1) to mu-opioid receptors. In animal models, M1 is up to 6 times more potent than tramadol in producing analgesia and 200 times more potent in mu-opioid binding. Tramadol-induced analgesia is only partially antagonized by the opiate antagonist naloxone in several animal tests. The relative contribution of both tramadol and M1 to human analgesia is dependent upon the plasma concentrations of each compound.

Tramadol has been shown to inhibit reuptake of norepinephrine and serotonin in vitro, as have some other opioid analgesics. These mechanisms may contribute independently to the overall analgesic profile of tramadol.

Apart from analgesia, tramadol hydrochloride administration may produce various symptoms (including dizziness, somnolence, nausea, constipation, sweating and pruritus) similar to that of other opioids. In contrast to morphine, tramadol has not been shown to cause histamine release. At therapeutic doses, tramadol has no effect on heart rate, left-ventricular function or cardiac index. Orthostatic hypotension has been observed.

Pharmacokinetics

The analgesic activity of tramadol hydrochloride is due to both parent drug and the M1 metabolite (See CLINICAL PHARMACOLOGY, Mechanism of Action).

RYZOLT™ is formulated as a racemate and both tramadol and M1 are detected in the circulation.

The pharmacokinetics of tramadol and M1 are dose-proportional over a 100 to 300 mg dose range in healthy subjects.

Absorption

The median time to peak plasma concentrations of tramadol and M1 after multiple-dose administration of RYZOLT™ 200 mg tablets to healthy subjects are attained at about 4 h and 5 h, respectively (Table 1 and Figure 1).

The pharmacokinetic parameter values for RYZOLT™ 200 mg administered once daily and tramadol immediate-release 50 mg administered every six hours are provided in Table 1. The relative bioavailability of a 200 mg RYZOLT™ tablet compared to a 50 mg immediate-release tablet dosed every six hours was approximately 95% in healthy subjects.

Steady-state plasma concentrations are reached within approximately 48 hours.

Figure 1.Mean Tramadol Plasma Concentrations at Steady State Following Five Days of Oral Administration of RYZOLT™ 200 mg Once Daily and Immediate-Release Tramadol 50 mg Every 6 Hours.

Figure 2. Mean M1 Plasma Concentrations at Steady State Following Five Days of Oral Administration of RYZOLT™ 200 mg Once Daily and Immediate-Release Tramadol 50 mg Every 6 Hours

Food Effect

Co-administration with a high fat meal did not significantly affect AUC (overall exposure to tramadol); however, Cmax (peak plasma concentration) increased 67% following a single 300 mg tablet administration and 54% following a single 200 mg tablet administration. RYZOLT™ was administered without regard to food in all clinical trials.

Distribution

The volume of distribution of tramadol is 2.6 and 2.9 L/kg in males and females, respectively, following a 100 mg intravenous dose. The binding of tramadol to human plasma proteins is approximately 20%. Protein binding also appears to be independent of concentration up to 10 µg/mL. Saturation of plasma protein binding occurs only at concentrations outside the clinically relevant range.

Metabolism

Tramadol is extensively metabolized after oral administration. The major metabolic pathways appear to be N- and O-demethylation and glucuronidation or sulfation in the liver. N-demethylation is mediated by CYP3A4 and CYP2B6. One metabolite (O-desmethyltramadol, denoted M1) is pharmacologically active in animal models. Formation of M1 is dependent on CYP2D6 and as such is subject to inhibition and polymorphism, which may affect the therapeutic response (See PRECAUTIONS - Drug Interactions).

Elimination

Tramadol is eliminated primarily through metabolism by the liver and the metabolites are eliminated primarily by the kidneys. Approximately 30% of the dose is excreted in the urine as unchanged drug, whereas 60% of the dose is excreted as metabolites. The remainder is excreted either as unidentified or as unextractable metabolites. After single administration of RYZOLT™, the mean terminal plasma elimination half-lives of racemic tramadol and racemic M1 are 6.5 ± 1.5 and 7.5 ± 1.4 hours, respectively.

Special Populations Renal Impairment

Impaired renal function results in a decreased rate and extent of excretion of tramadol and its active metabolite, M1 in patients taking an immediate-release formulation of tramadol. RYZOLT™ has not been studied in patients with renal impairment. The limited availability of dose strengths and once daily dosing of RYZOLT™ do not permit the dosing flexibility required for safe use in patients with severe renal impairment. Therefore, RYZOLT™ should not be used in patients with severe renal impairment (creatinine clearance less than 30 mL/min) (See WARNINGS, Use in Renal and Hepatic Disease and DOSAGE AND ADMINISTRATION). The total amount of tramadol and M1 removed during a 4-hour dialysis period is less than 7% of the administered dose.

Hepatic Impairment

The metabolism of tramadol and M1 is reduced in patients with advanced cirrhosis of the liver, resulting in both a larger area under the concentration time curve (AUC) for tramadol and longer mean tramadol and M1 elimination half-lives (13 hours for tramadol and 19 hours for M1) after the administration of tramadol immediate-release tablets. RYZOLT™ has not been studied in patients with hepatic impairment. The limited availability of dose strengths and once daily dosing of RYZOLT™ do not permit the dosing flexibility required for safe use in patients with hepatic impairment. Therefore, RYZOLT™ should not be used in patients with hepatic impairment (see WARNINGS, Use in Renal and Hepatic Disease and DOSAGE AND ADMINISTRATION).

Geriatric Patients

Healthy elderly subjects aged 65 to 75 years administered an immediate-release formulation of tramadol, have plasma concentrations and elimination half-lives comparable to those observed in healthy subjects less than 65 years of age. In subjects over 75 years, mean maximum plasma concentrations are elevated (208 vs. 162 ng/mL) and the mean elimination half-life is prolonged (7 vs. 6 hours) compared to subjects 65 to 75 years of age. Adjustment of the daily dose is recommended for patients older than 75 years (See DOSAGE AND ADMINISTRATION).

Gender

Following a 100 mg IV dose of tramadol, plasma clearance was 6.4 mL/min/kg in males and 5.7 mL/min/kg in females. Following a single oral dose of immediate-release tramadol, and after adjusting for body weight, females had a 12% higher peak tramadol concentration and a 35% higher area under the concentration-time curve compared to males. The clinical significance of this difference is unknown.

Drug Interactions

The formation of the active metabolite of tramadol, M1, is mediated by CYP2D6, a polymorphic enzyme. Approximately 7% of the population has reduced activity of CYP2D6. These individuals are "poor metabolizers" of debrisoquine, dextromethorphan and tricyclic antidepressants, among other drugs. In studies in healthy subjects administered immediate-release tramadol products, concentrations of tramadol were approximately 20% higher in "poor metabolizers" versus "extensive metabolizers", while M1 concentrations were 40% lower. In vitro drug interaction studies in human liver microsomes indicate that inhibitors of CYP2D6 (amitriptyline, quinidine and fluoxetine and its metabolite norfluoxetine,) inhibit the metabolism of tramadol to various degrees, suggesting that concomitant administration of these compounds could result in increases in tramadol concentrations and decreased concentrations of M1. The full pharmacological impact of these alterations in terms of either efficacy or safety is unknown.

Tramadol is also metabolized by CYP3A4. Administration of CYP3A4 inhibitors, such as ketoconazole and erythromycin, or inducers, such as rifampin and St. John’s Wort, with RYZOLT™ may affect the metabolism of tramadol leading to altered tramadol exposure (see PRECAUTIONS).

Quinidine

Quinidineis a selective inhibitor of CYP2D6, so that concomitant administration of quinidine and RYZOLT™ may result in increased concentrations of tramadol and reduced concentrations of M1. The clinical consequences of these findings are unknown (see PRECAUTIONS). In vitro drug interaction studies in human liver microsomes indicate that tramadol has no effect on quinidine metabolism.

Carbamazepine

Carbamazepine, a CYP3A4 inducer, increases tramadol metabolism. Patients taking carbamazepine may have a significantly reduced analgesic effect of tramadol. Because of the seizure risk associated with tramadol, concomitant administration of RYZOLT™ and carbamazepine is not recommended (see PRECAUTIONS).

Cimetidine

Concomitant administration of tramadol immediate-release tablets with cimetidine does not result in clinically significant changes in tramadol pharmacokinetics. No alteration of the RYZOLT™ dosage regimen with cimetidine is recommended.

Clinical Studies

RYZOLT™ was studied in four 12-week, randomized, double-blind, controlled studies in patients with moderate to severe pain due to osteoarthritis. Efficacy was demonstrated in one double-blind, placebo-controlled, randomized withdrawal design study. In this study, patients who experienced a reduction of pain and were able to tolerate RYZOLT™ during an open-label titration period, were then randomized to RYZOLT™ or to placebo for 12 weeks. Sixty-five percent of patients were able to successfully titrate onto RYZOLT™. After a washout, patients randomized to RYZOLT™ were titrated to 200 mg or 300 mg of RYZOLT™ based on tolerability and remained on that dose for the following 12-week period. Approximately 24% of patients discontinued during the randomized period of the study, with more patients discontinuing from the RYZOLT™ arm than the placebo arm due to adverse events (10% vs. 5%, respectively) and more patients discontinuing from the placebo arm than the RYZOLT™ arm due to lack of efficacy (10% vs. 8%, respectively). Patients treated with RYZOLT™ demonstrated a greater improvement in pain intensity, measured on an 11-point numerical rating scale, at the end of treatment compared to patients randomized to placebo. Figure 3 shows the fraction of patients achieving various degree of improvement in pain from baseline to the end of treatment (week 12). The figure is cumulative, so that patients whose change from baseline is, for example, 50%, are also included at every level of improvement below 50%. Patients who did not complete the study were assigned 0% improvement.

Figure 3. Proportion of Patients Achieving Various Levels of Pain Relief as Measured by 12-Week Pain Intensity.

Indications and Usage

RYZOLT™ is indicated for the management of moderate to moderately severe chronic pain in adults who require around-the-clock treatment of their pain for an extended period of time.

Contraindications

RYZOLT™ should not be administered to patients who have previously demonstrated hypersensitivity to tramadol, any other component of this product or opioids.

Warnings

Seizure Risk

Seizures have been reported in patients receiving tramadol hydrochloride within the recommended dosage range. Spontaneous postmarketing reports indicate that seizure risk is increased with doses above the recommended range. Concomitant use of tramadol hydrochloride increases the seizure risk in patients taking:

- Selective serotonin reuptake inhibitors (SSRI antidepressants or anorectics),
- Tricyclic antidepressants (TCAs), and other tricyclic compounds (e.g., cyclobenzaprine, promethazine, etc.), or
- Other opioids.

Administration of RYZOLT™ may enhance the seizure risk in patients taking:

- Monoamine Oxidase (MAO) inhibitors (See also WARNINGS – Use with MAO Inhibitors and Serotonin Re-uptake Inhibitors),
- Neuroleptics, or
- Other drugs that reduce the seizure threshold.

Risk of convulsions may also be increased in patients with epilepsy, those with a history of seizures, or in patients with a recognized risk for seizure (such as head trauma, certain metabolic disorders, alcohol and drug withdrawal and CNS infections). In tramadol overdose, naloxone administration may increase the risk of seizures.

Suicide Risk

Do not prescribe RYZOLT™ for patients who are suicidal or addiction-prone. Prescribe RYZOLT™ with caution for patients taking tranquilizers or antidepressant drugs and for patients who use alcohol in excess. Serious potential consequences of overdosage with RYZOLT™ are central nervous system depression, respiratory depression and death. In treating an overdose, primary attention should be given to maintaining adequate ventilation along with general supportive treatment (see OVERDOSAGE).

Serotonin Syndrome Risk

The development of a potentially life-threatening serotonin syndrome may occur with the use of tramadol products, including RYZOLT™, particularly with concomitant use of serotonergic drugs such as SSRIs, SNRIs, TCAs, MAOIs, and triptans, with drugs which impair metabolism of serotonin (including MAOIs), and with drugs which impair metabolism of tramadol (CYP2D6 and CYP3A4 inhibitors). This may occur within the recommended dose (see CLINICAL PHARMACOLOGY, Pharmacokinetics).

Serotonin syndrome may include mental-status changes (e.g., agitation, hallucinations, coma), autonomic instability (e.g., tachycardia, labile blood pressure, hyperthermia), neuromuscular aberrations (e.g., hyperreflexia, incoordination) and/or gastrointestinal symptoms (e.g., nausea, vomiting, diarrhea).

Tramadol products in excessive doses, either alone or in combination with other Central Nervous System (CNS) depressants, including alcohol, are a major cause of drug-related deaths. Fatalities within the first hour of overdosage are not uncommon. Tramadol should not be taken in doses higher than those recommended by the physician. The judicious prescribing of tramadol is essential to the safe use of this drug. With patients who are depressed or suicidal, consideration should be given to the use of non-narcotic analgesics. Patients should be cautioned about the concomitant use of tramadol products and alcohol because of potentially serious CNS-additive effects of these agents. Because of its added depressant effects, tramadol should be prescribed with caution for those patients whose medical condition requires the concomitant administration of sedatives, tranquilizers, muscle relaxants, antidepressants, or other CNS-depressant drugs. Patients should be advised of the additive depressant effects of these combinations.

Many of the tramadol-related deaths have occurred in patients with previous histories of emotional disturbances or suicidal ideation or attempts as well as histories of misuse of tranquilizers, alcohol, and other CNS-active drugs. Some deaths have occurred as a consequence of the accidental ingestion of excessive quantities of tramadol alone or in combination with other drugs. Patients taking tramadol should be warned not to exceed the dose recommended by their physician.

Anaphylactoid Reactions

Serious and rarely fatal anaphylactoid reactions have been reported in patients receiving therapy with tramadol. When these events do occur, it is often following the first dose. Other reported allergic reactions include pruritus, hives, bronchospasm, angioedema, toxic epidermal necrolysis and Stevens-Johnson syndrome. Patients with a history of anaphylactoid reactions to other opioids may be at increased risk and therefore should not receive RYZOLT™ (See CONTRAINDICATIONS).

Respiratory Depression

RYZOLT™ should be administered cautiously in patients at risk for respiratory depression. In these patients, alternative non-opioid analgesics should be considered. When large doses of tramadol are administered with anesthetic medications or alcohol, respiratory depression may result. Respiratory depression should be treated as an overdose. If naloxone is to be administered, use cautiously because it may precipitate seizures (See WARNINGS, Seizure Risk and OVERDOSAGE).

Interaction with Central Nervous System (CNS) Depressants

RYZOLT™ should be used with caution and in reduced dosages when administered to patients receiving CNS depressants such as alcohol, opioids, anesthetic agents, narcotics, phenothiazines, tranquilizers or sedative hypnotics. Tramadol increases the risk of CNS and respiratory depression in these patients.

Increased Intracranial Pressure or Head Trauma

RYZOLT™ should be used with caution in patients with increased intracranial pressure or head injury. The respiratory depressant effects of opioids include carbon dioxide retention and secondary elevation of cerebrospinal fluid pressure, and may be markedly exaggerated in these patients. Additionally, pupillary changes (miosis) from tramadol may obscure the existence, extent, or course of intracranial pathology. Clinicians should also maintain a high index of suspicion for adverse drug reaction when evaluating altered mental status in these patients if they are receiving RYZOLT™ (See Respiratory Depression).

Use in Ambulatory Patients

RYZOLT™ may impair the mental and physical abilities required for the performance of potentially hazardous tasks such as driving a car or operating machinery. Patients using this drug should be cautioned accordingly.

Use with MAO Inhibitors and Serotonin Re-uptake Inhibitors

RYZOLT™ should be used with great caution in patients taking MAO inhibitors. Animal studies have shown increased deaths with combined administration of tramadol and MAO inhibitors. Concomitant use of tramadol products with MAO inhibitors or SSRIs increases the risk of adverse events, including seizure and serotonin syndrome.

Withdrawal

Withdrawal symptoms may occur if RYZOLT™is discontinued abruptly. These symptoms may include: anxiety, sweating, insomnia, rigors, pain, nausea, tremors, diarrhea, upper respiratory symptoms, piloerection, and rarely hallucinations.

In a 12 week study, 325 patients were followed for 3 and 7 days after discontinuation of treatment with RYZOLT™. The majority of reported post-treatment adverse events including withdrawal symptoms were mild to moderate in nature. Onset of the post-treatment adverse events occurred more frequently within the first three days after treatment was stopped. Less than 1% of patients taking RYZOLT™ met the DSM-IV criteria for a diagnosis of opioid withdrawal.

Clinical experience suggests that signs and symptoms of withdrawal may be reduced by tapering medication when discontinuing tramadol therapy.

Misuse, Abuse and Diversion of Opioids

Tramadol is an opioid agonist of the morphine type. Such drugs are sought by drug abusers and people with addiction disorders and are subject to criminal diversion.

Like other opioid agonists, legal or illicit, tramadol can be abused. This should be considered when prescribing or dispensing RYZOLT™in situations where the healthcare professional is concerned about a risk of misuse, abuse, or diversion.

RYZOLT™ could be abused by breaking, crushing, chewing, or dissolving the product which can result in the uncontrolled delivery of the opioid, and as a consequence poses a significant risk of overdose and death.

Concerns about abuse, addiction, and diversion should not prevent the proper management of pain.

Healthcare professionals should contact their State Professional Licensing Board or State Controlled Substances Authority for information on how to prevent and detect abuse or diversion of this product.

Interactions with Alcohol and Drugs of Abuse

Tramadol may be expected to have additive effects when used in conjunction with alcohol, other opioids or drugs, whether legal or illicit, which cause central nervous system depression.

Drug Abuse and Addiction Abuse

RYZOLT™ is a mu-agonist opioid. Tramadol, like other opioids used in analgesia, can be abused and is subject to criminal diversion.

Addiction is a primary, chronic, neurobiologic disease, with genetic, psychosocial, and environmental factors influencing its development and manifestations. It is characterized by behaviors that include one or more of the following: impaired control over drug use, compulsive use, continued use despite harm, and craving. Drug addiction is a treatable disease, utilizing a multidisciplinary approach, but relapse is common.

Concerns about abuse and addiction should not prevent the proper management of pain. However all patients treated with opioids require careful monitoring for signs of abuse and addiction, because use of opioid analgesic products carries the risk of addiction even under appropriate medical use.

“Drug-seeking” behavior is very common in addicts and drug abusers. Drug-seeking tactics include emergency calls or visits near the end of office hours, refusal to undergo appropriate examination, testing or referral, repeated “loss” of prescriptions, tampering with prescriptions and reluctance to provide prior medical records or contact information for other treating physician(s). “Doctor shopping” to obtain additional prescriptions is common among drug abusers and people suffering from untreated addiction.

Abuse and addiction are separate and distinct from physical dependence and tolerance. Physicians should be aware that addiction may not be accompanied by concurrent tolerance and symptoms of physical dependence in all addicts. In addition, abuse of opioids can occur in the absence of true addiction and is characterized by misuse for non-medical purposes, often in combination with other psychoactive substances. RYZOLT™, like other opioids, may be diverted for non-medical use. Careful record-keeping of prescribing information, including quantity, frequency, and renewal requests is strongly advised.

Proper assessment of the patient, proper prescribing practices, periodic re-evaluation of therapy, and proper dispensing and storage are appropriate measures that help to limit abuse of opioid drugs.

RYZOLT™ is intended for oral use only. The crushed tablet poses a hazard of overdose and death. This risk is increased with concurrent abuse of alcohol and other substances. With parenteral abuse, the tablet excipients can be expected to result in local tissue necrosis, infection, pulmonary granulomas, and increased risk of endocarditis and valvular heart injury. Parenteral drug abuse is commonly associated with transmission of infectious diseases such as hepatitis and HIV.

Dependence

Tolerance is the need for increasing doses of opioids to maintain a defined effect such as analgesia (in the absence of disease progression or other external factors). Physical dependence is manifested by withdrawal symptoms after abrupt discontinuation of a drug or upon administration of an antagonist.

The opioid abstinence or withdrawal syndrome is characterized by some or all of the following: restlessness, lacrimation, rhinorrhea, yawning, perspiration, chills, myalgia, and mydriasis. Other symptoms also may develop, including irritability, anxiety, backache, joint pain, weakness, abdominal cramps, insomnia, nausea, anorexia, vomiting, diarrhea, or increased blood pressure, respiratory rate, or heart rate. Generally, tolerance and/or withdrawal are more likely to occur the longer a patient is on continuous opioid therapy.

Risk of Overdosage

Serious potential consequences of overdosage with RYZOLT™ are central nervous system depression, respiratory depression and death. In treating an overdose, primary attention should be given to maintaining adequate ventilation along with general supportive treatment (See OVERDOSAGE).

Precautions Acute Abdominal Conditions

The administration of RYZOLT™ may complicate the clinical assessment of patients with acute abdominal conditions.

Use in Renal and Hepatic Disease

Impaired renal function results in a decreased rate and extent of excretion of tramadol and its active metabolite, M1 in patients taking an immediate-release formulation of tramadol. RYZOLT™ has not been studied in patients with renal impairment. The limited availability of dose strengths and once daily dosing of RYZOLT™ do not permit the dosing flexibility required for safe use in patients with severe renal impairment. Therefore, RYZOLT™ should not be used in patients with severe renal impairment (see CLINICAL PHARMACOLOGY and DOSAGE AND ADMINISTRATION).

The metabolism of tramadol and M1 is reduced in patients with advanced cirrhosis of the liver. RYZOLT™ has not been studied in patients with hepatic impairment. The limited availability of dose strengths and once daily dosing of RYZOLT™ do not permit the dosing flexibility required for safe use in patients with hepatic impairment. Therefore, RYZOLT™ should not be used in patients with hepatic impairment (seeCLINICAL PHARMACOLOGYand DOSAGE AND ADMINISTRATION).

Adverse Reactions

RYZOLT™was administered to a total of 2707 subjects (2406 patients and 301 healthy volunteers) during clinical studies, including four randomized double-blind studies (treatment ≥ 12 weeks) and two open-label long-term studies (treatment up to 12 months) in patients with moderate to severe pain due to osteoarthritis of the knee. A total of 844 patients were exposed to RYZOLT™for 12 weeks, 493 patients for 6 months and 243 patients for 12 months. Treatment emergent adverse events increased with dose from 100 mg to 300 mg in the three twelve-week, randomized, double-blind, placebo-controlled studies.

The majority of patients who experienced the most common adverse events (≥5%) reported mild to moderate symptoms. Less than 3% of adverse events were rated as severe. Overall, onset of these adverse events usually occurred within the first two weeks of treatment.

Adverse reactions with an incidence of 1.0% to less than 5.0%

Ear and labyrinth disorders: vertigo

Gastrointestinal disorders: abdominal pain, diarrhea, dry mouth, dyspepsia, upper abdominal pain

General disorders: fatigue, weakness

Investigations: weight decreased

Metabolism and nutrition disorders: anorexia

Musculoskeletal and connective tissue disorders: arthralgia

Nervous system disorders: headache, tremor

Psychiatric disorders: anxiety, insomnia

Skin and subcutaneous tissue disorders: pruritus, sweating increased

Vascular disorders: hot flushes

Adverse reactions with an incidence of less than 1.0%

Blood and lymphatic system disorders: anemia, thrombocytopenia

Cardiac disorders: bradycardia

Eye disorders: blurred vision, visual disturbance

Gastrointestinal disorders: abdominal discomfort, abdominal distension, abdominal tenderness, change in bowel habit, constipation aggravated, diverticulitis, diverticulum, dyspepsia aggravated, dysphagia, fecal impaction, gastric irritation, gastritis, gastrointestinal hemorrhage, gastrointestinal irritation, gastro-esophageal reflux disease, lower abdominal pain, pancreatitis aggravated, rectal hemorrhage, rectal prolapse, retching

General disorders: asthenia, malaise

Hepatobiliary disorders: biliary tract disorder, cholelithiasis

Immune system disorders: hypersensitivity

Investigations: alanine aminotransferase decreased, alanine aminotransferase increased, aspartate aminotransferase decreased, aspartate aminotransferase increased, blood amylase increased, blood creatinine increased, blood in stool, blood potassium abnormal, blood pressure increased gamma glutamyltransferase increased

Metabolism and nutrition disorders: appetite decreased, dehydration

Nervous system disorders: ataxia, disturbance in attention, dysarthria, gait abnormal, headache aggravated, mental impairment, sedation, seizure, sleep apnea syndrome, syncope, tremor

Psychiatric disorders: abnormal behavior, agitation, anxiety, confusion, depression, emotional disturbance, euphoric mood, indifference, irritability, libido decreased, nervousness, sleep disorder

Renal and urinary disorders: difficulty in micturition, urinary hesitation, urinary retention

Reproductive system and breast disorders: erectile dysfunction, sexual dysfunction

Respiratory, thoracic and mediastinal disorders: dyspnea

Skin and subcutaneous tissue disorders: allergic dermatitis, cold sweat, dermatitis, night sweats, pallor, generalized pruritus, urticaria

Vascular disorders: flushing, hypertension, hypotension, orthostatic hypotension

Overdosage

Acute overdosage with tramadol can be manifested by respiratory depression, somnolence progressing to stupor or coma, skeletal muscle flaccidity, cold and clammy skin, constricted pupils, bradycardia, hypotension and death.

Death due to overdose have been reported with abuse and misuse of tramadol, by ingesting, inhaling, or injecting the crushed tablets. The risk of fatal overdose is further increased when tramadol is abused concurrently with alcohol and other CNS depressants, including other opioids.

In the treatment of tramadol overdosage, primary attention should be given to the re-establishment of a patent airway and institution of assisted or controlled ventilation. Supportive measures (including oxygen and vasopressors) should be employed in the management of circulatory shock and pulmonary edema accompanying overdose as indicated. Cardiac arrest or arrhythmias may require cardiac massage or defibrillation.

While naloxone will reverse some (but not all) symptoms caused by overdosage with tramadol, the risk of seizures is also increased with naloxone administration. In animals, convulsions following the administration of toxic doses of tramadol could be suppressed with barbiturates or benzodiazepines but were increased with naloxone. Naloxone administration did not change the lethality of an overdose in mice. Hemodialysis is not expected to be helpful in an overdose because it removes less than 7% of the administered dose in a 4-hour dialysis period.

Dosage and Administration

RYZOLT™ extended-release tablets should be taken once a day. The tablets should be swallowed whole with liquid and not split, chewed, dissolved or crushed. RYZOLT™ tablets produce a continuous release of active ingredient over 24 hours: a repeat dosage within 24 hours is not recommended.

Patients Not Currently on Tramadol Immediate-Release Products:

Treatment with RYZOLT™ should be initiated at a dose of 100 mg/day. Daily doses should be titrated by 100 mg/day increments every 2-3 days (i.e., start 200 mg/day on day 3 or 4 of therapy) to achieve a balance between adequate pain control and tolerability for the individual patient. For patients requiring the 300 mg daily dose, titration should take at least 4 days (i.e. 300 mg/day on day 5). The usual daily dose is 200 or 300 mg. The daily dose and titration should be individualized for each patient. Therapy should be continued with the lowest effective dose. RYZOLT™should not be administered at a dose exceeding 300 mg per day.

Clinical experience suggests that signs and symptoms of withdrawal may be reduced by tapering medication when discontinuing tramadol therapy.

Patients Currently on Tramadol Immediate-Release Products:

For patients maintained on tramadol immediate release (IR) products, the 24-hour tramadol IR dose should be calculated and the patient should be initiated on a total daily dose of RYZOLT™rounded down to the next lowest 100 mg increment. The dose may subsequently be individualized according to patient need. Due to limitations in flexibility of dose selection with RYZOLT™, some patients maintained on tramadol IR products may not be able to convert to RYZOLT™. RYZOLT™should not be administered at a dose exceeding 300 mg per day. Do not use RYZOLT™ with other tramadol products. (see WARNINGS).

Individualization of Dose

Good pain management practice dictates that analgesic dose be individualized according to patient need using the lowest beneficial dose. Studies with tramadol products in adults have shown that starting at the lowest possible dose and titrating upward will result in fewer discontinuations and increased tolerability.

Renal and Hepatic Disease

RYZOLT™ should not be used in patients with:

- Creatinine clearance less than 30 mL/min,
- Hepatic impairment.

(See WARNINGS, Use in Renal and Hepatic Disease).

Geriatric patients (65 years of age and older)

In general, dose selection for patients over 65 years of age who may have decreased hepatic or renal function, or other concomitant diseases, should be initiated cautiously, usually starting at the low end of the dosing range. RYZOLT™ should be administered with greater caution at the lowest effective dose in patients over 75 years, due to the potential for greater frequency of adverse events in this population.

How Supplied

RYZOLT™ (tramadol hydrochloride extended-release tablets) are supplied in a number of packages and dose strengths:

100-mg, white, beveled edge, round biconvex tablets, plain on one side and printed "PP 100" in black ink on the other side.

Bottle of 30 tablets – NDC 59011-334-30

Bottle of 90 tablets – NDC 59011-334-90

200-mg, white, beveled edge, round biconvex tablets, plain on one side and printed "PP 200" in black ink on the other side

Bottle of 30 tablets – NDC 59011-335-30

Bottle of 90 tablets – NDC 59011-335-90

300-mg, white, beveled edge, round biconvex tablets, plain on one side and printed "PP 300" in black ink on the other side

Bottle of 30 tablets – NDC 59011-336-30

Bottle of 90 tablets – NDC 59011-336-90

Store at 25°C (77°F); excursions permitted between 15-30°C (59 – 86°F). Dispense in a tight, light-resistant container.

Warning: keep out of reach of children.

Manufactured by:

Confab Laboratories Inc

Saint-Hubert, Quebec, Canada J3Y 3X3

Distributed by:

Purdue Pharma L.P.

Stamford, CT 06901-3431

Licensed from Labopharm Europe Limited

U.S. Patent 6,607,748; U.S. Patent 5,591,452; U.S. Patent 6,254,887

RYZOLTTM is a trademark of Purdue Pharma L.P.

Information for Patients Patients should be instructed that:

- RYZOLT™ is for oral use only and should be swallowed whole with a sufficient quantity of liquid and not split, chewed, dissolved or crushed.
- RYZOLT™ may cause seizures and/or serotonin syndrome with concomitant use of serotonergic agents (including SSRIs, SNRIs and triptans) or drugs that significantly reduce the metabolic clearance of tramadol.
- RYZOLT™should be taken once daily, at approximately the same time every day and that exceeding these instructions can result in respiratory depression, seizures or death.
- RYZOLT™should not be taken in doses exceeding the maximum recommended daily dose as exceeding these recommendations can result in respiratory depression, seizures or even death (See DOSAGE AND ADMINISTRATION)
- RYZOLT™may impair the mental and physical abilities required for the performance of potentially hazardous tasks such as driving a car or operating machinery. Patients using this drug should be cautioned accordingly.
- RYZOLT™should not be taken with alcohol-containing beverages.
- RYZOLT™should be used with caution when taking medications such as tranquilizers, hypnotics or other opiate containing analgesics.
- Female patients should be instructed to inform the physician if they are pregnant, think they might become pregnant, or are trying to become pregnant (See PRECAUTIONS - Pregnancy and Labor and Delivery).
- Clinical experience suggests that signs and symptoms of withdrawal may be reduced by tapering medication when discontinuing tramadol therapy.
- Patients should be informed to keep RYZOLT™out of reach of children.

Use in Drug and Alcohol Addiction

RYZOLT™ is an opioid with no approved use for the management of addictive disorders. Its proper usage in individuals with drug or alcohol dependence, either active or in remission is for the management of pain requiring opioid analgesia.

Drug Interactions

CYP2D6 and CYP3A4 Inhibitors: Concomitant administration of CYP2D6 and/or CYP3A4 inhibitors (see CLINICAL PHARMACOLOGY, Pharmacokinetics), such as quinidine, fluoxetine, paroxetine and amitriptyline (CYP2D6 inhibitors), and ketoconazole and erythromycin (CYP3A4 inhibitors), may reduce metabolic clearance of tramadol increasing the risk for serious adverse events including seizures and serotonin syndrome.

Serotonergic Drugs: There have been postmarketing reports of serotonin syndrome with use of tramadol and SSRIs/SNRIs or MAOIs and α2-adrenergic blockers. Caution is advised when RYZOLT™ is coadministered with other drugs that may affect the serotonergic neurotransmitter systems, such as SSRIs, MAOIs, triptans, linezolid (an antibiotic which is a reversible non-selective MAOI), lithium, or St. John’s Wort. If concomitant treatment of RYZOLT™ with a drug affecting the serotonergic neurotransmitter system is clinically warranted, careful observation of the patient is advised, particularly during treatment initiation and dose increases (see WARNINGS, Serotonin Syndrome).

Triptans: Based on the mechanism of action of tramadol and the potential for serotonin syndrome, caution is advised when RYZOLT™is coadministered with a triptan. If concomitant treatment of RYZOLT™with a triptan is clinically warranted, careful observation of the patient is advised, particularly during treatment initiation and dose increases (see WARNINGS, Serotonin Syndrome).

Use with Carbamazepine

Patients taking carbamazepine, a CYP3A4inducer, may have a significantly reduced analgesic effect. Because carbamazepine increases tramadol metabolism and because of the seizure risk associated with tramadol, concomitant administration of RYZOLT™and carbamazepine is not recommended.

Use with Quinidine

Tramadol is metabolized to M1 by CYP2D6. Quinidineis a selective inhibitor of that isoenzyme, so that concomitant administration of quinidine and tramadol products results in increased concentrations of tramadol and reduced concentrations of M1. The clinical consequences of these findings are unknown. In vitro drug interaction studies in human liver microsomes indicate that tramadol has no effect on quinidine metabolism.

Use with Digoxin and Warfarin

Post-marketing surveillance of tramadol has revealed rare reports of digoxin toxicity and alteration of warfarin effect, including elevation of prothrombin times.

Interaction With Central Nervous System (CNS) Depressants

RYZOLT™ should be used with caution and in reduced dosages when administered to patients receiving CNS depressants such as alcohol, opioids, anesthetic agents, narcotics, phenothiazines, tranquilizers or sedative hypnotics. RYZOLT™ increases the risk of CNS and respiratory depression in these patients.

Potential of Other Drugs to Affect Tramadol

In vitro drug interaction studies in human liver microsomes indicate that concomitant administration with inhibitors of CYP2D6 such as fluoxetine, paroxetine, and amitriptyline could result in some inhibition of the metabolism of tramadol.

Tramadol is partially metabolized by CYP3A4. Administration of CYP3A4 inhibitors, such as ketoconazole and erythromycin, or inducers, such as rifampin and St. John’s Wort, with RYZOLT™may affect the metabolism of tramadol leading to altered tramadol exposure.

Potential for Tramadol to Affect Other Drugs

In vitro studies indicate that tramadol is unlikely to inhibit the CYP3A4-mediated metabolism of other drugs when administered concomitantly at therapeutic doses. Tramadol is a mild inducer of selected drug metabolism pathways measured in animals.

Carcinogenesis, Mutagenesis and Impairment of Fertility

A slight, but statistically significant increase in two common murine tumors, pulmonary and hepatic, was observed in a mouse carcinogenicity study, particularly in aged mice. Mice were dosed orally up to 30 mg/kg (90 mg/m^2 or 0.5 times the maximum daily human dosage of 185 mg/m^2) for approximately two years, although the study was not done with the Maximum Tolerated Dose. This finding is not believed to suggest risk in humans. No such finding occurred in a rat carcinogenicity study (dosing orally up to 30 mg/kg - 180 mg/m^2 equal to the maximum daily human dosage of tramadol).

Tramadol was not mutagenic in the following assays: Ames Salmonella microsomal activation test, CHO/HPRT mammalian cell assay, mouse lymphoma assay (in the absence of metabolic activation), dominant lethal mutation tests in mice, chromosome aberration test in Chinese hamsters, and bone marrow micronucleus tests in mice and Chinese hamsters. Positive mutagenic results occurred in the presence of metabolic activation in the mouse lymphoma assay and micronucleus test in rats. Relevance of the finding in humans is unknown.

No effects on fertility were observed for tramadol at oral dose levels up to 50 mg/kg (300 mg/m^2) in male rats and 75 mg/kg (450 mg/m^2) in female rats. These dosages are 1.6 and 2.4 times the maximum daily human dosage of 185 mg/m^2, respectively.

Pregnancy

Teratogenic Effects: Pregnancy Category C

Tramadol has been shown to be embryotoxic and fetotoxic in mice, (120 mg/kg or 360 mg/m^2), rats (≥25 mg/kg or 150 mg/m^2) and rabbits (≥75mg/kg or 900 mg/m^2) at maternally toxic dosages, but was not teratogenic at these dose levels. These dosages on an mg/m^2 basis are 1.9, 0.8 and 4.9 times the maximum daily human dosage (185 mg/m^2) for mouse, rat and rabbit, respectively.

No drug related teratogenic effects were observed in progeny of mice (up to 140 mg/kg or 420 mg/m^2), rats (up to 80 mg/kg or 480 mg/m^2) or rabbits (up to 300 mg/kg or 3600 mg/m^2) treated with tramadol by various routes. Embryo and fetal toxicity consisted primarily of decreased fetal weights, skeletal ossification and increased supernumerary ribs in maternally toxic dose levels. Transient delays in developmental or behavioral parameters were also seen in pups from rat dams allowed to deliver. Embryo and fetal lethality were reported only in one rabbit study at 300 mg/kg (3600 mg/m^2), a dose that would cause extreme maternal toxicity in the rabbit. The dosages listed for mouse, rat and rabbit are 2.2, 2.6 and 19.4 times the maximum daily human dosage (185 mg/m^2), respectively.

Non-teratogenic Effects

Tramadol was evaluated in peri- and post-natal studies in rats. Progeny of dams receiving oral (gavage) dose levels of 50 mg/kg (300 mg/m^2 or 1.6 times the maximum daily human RYZOLT dosage) or greater had decreased weights, and pup survival was decreased early in lactation at 80 mg/kg (480 mg/m^2 or 2.6 times the maximum daily human dose).

There are no adequate and well-controlled studies in pregnant women. RYZOLT™ should be used during pregnancy only if the potential benefit justifies the potential risk to the fetus. Neonatal seizures, neonatal withdrawal syndrome, fetal death and stillbirth have been reported during post-marketing surveillance of tramadol immediate-release products.

Labor and Delivery

RYZOLT™ should not be used in pregnant women prior to or during labor unless the potential benefits outweigh the risks. Safe use in pregnancy has not been established. Chronic use during pregnancy may lead to physical dependence and post-partum withdrawal symptoms in the newborn (See DRUG ABUSE AND ADDICTION). Tramadol has been shown to cross the placenta. The mean ratio of serum tramadol in the umbilical veins compared to maternal veins was 0.83 for 40 women given tramadol during labor.

The effect of RYZOLT™, if any, on the later growth, development and functional maturation of the child is unknown.

Nursing Mother

RYZOLT™is not recommended for obstetrical preoperative medication or for post-delivery analgesia in nursing mothers because its safety in infants and newborns has not been studied. Following a single IV 100 mg dose of tramadol, the cumulative excretion in breast milk within 16 hours postdose was 100 µg of tramadol (0.1% of the maternal dose) and 27 µg of M1.

Pediatric Use

The safety and efficacy of RYZOLT™in patients under 16 years of age has not been established. The use of RYZOLT™in the pediatric population is not recommended.

Geriatric Use

In general, caution should be used when selecting the dose for an elderly patient. Usually, dose administration should start at the low end of the dosing range, reflecting the greater frequency of decreased hepatic, renal or cardiac function and of concomitant disease or other drug therapy (See CLINICAL PHARMACOLOGY and DOSAGE AND ADMINISTRATION).

In 12-week clinical trials, RYZOLT™was administered to 534 patients aged 65 years and older. Of those, 68 patients were 75 years of age and older. Comparable incidence rates of patients experiencing adverse events were observed for patients older than 65 years of age compared with younger patients (less than 65 years of age), except constipation for which the incidence was higher in older patients. RYZOLT™should be used with caution in patients older than 75 years of age (See CLINICAL PHARMACOLOGY and DOSAGE AND ADMINISTRATION).

Ryzolt Label

RYZOLT 100MG LABEL IMAGE

RYZOLT 300MG LABEL IMAGE